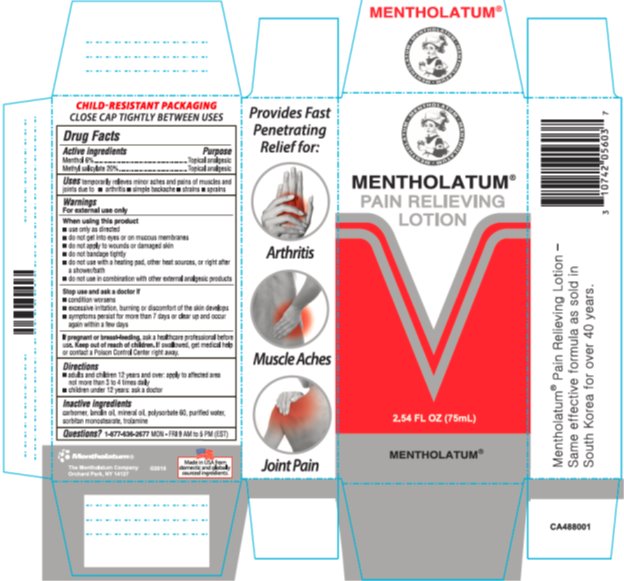 DRUG LABEL: Mentholatum Pain Relieving
NDC: 10742-8169 | Form: LOTION
Manufacturer: The Mentholatum Company
Category: otc | Type: HUMAN OTC DRUG LABEL
Date: 20241217

ACTIVE INGREDIENTS: MENTHOL, UNSPECIFIED FORM 60 mg/1 mL; METHYL SALICYLATE 200 mg/1 mL
INACTIVE INGREDIENTS: CARBOXYPOLYMETHYLENE; LANOLIN OIL; MINERAL OIL; POLYSORBATE 60; WATER; SORBITAN MONOSTEARATE; TROLAMINE

Drug Facts - Mentholatum Pain Relieving

Active ingredients

Menthol 6%

Methyl salicylate 20%

Purpose

Menthol - Topical analgesic

Methyl salicylate - Topical analgesic

Uses

temporarily relieves minor aches and pains of muscles and joints due to

- arthritis
- simple backache
- strains
- sprains

Warnings

When using this product

- use only as directed
- do not get into eyes or on mucous membranes
- do not apply to wounds or to damaged skin
- do not bandage tightly
- do not use with a heating pad, other heat sources, or right after a shower/bath
- do not use in combination with other external analgesic products

Stop use and ask a doctor if

- condition worsens
- excessive irritation, burning or discomfort of the skin develops
- symptoms persist for more than 7 days or clear up and occur again within a few days

If pregnant or breast-feeding,

ask a healthcare professional before use.

Keep Out of Reach of Children.

If swallowed, get medical help or contact a Poison Control Center right away.

Directions

- adults and children 12 years and over: apply to affected area not more than 3 to 4 times daily
- children under 12 years: ask a doctor

Inactive ingredients

carbomer, lanolin oil, polysorbate 60, purified water, sorbitan monosterate, trolamine